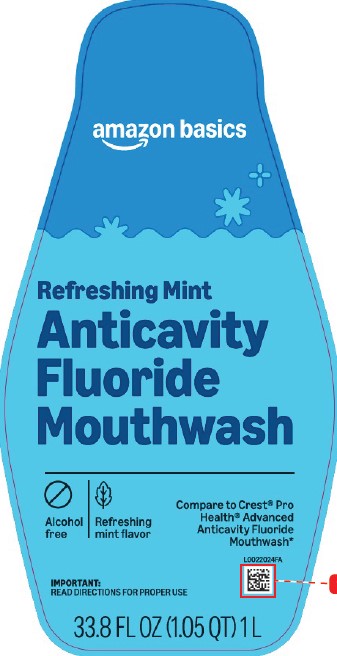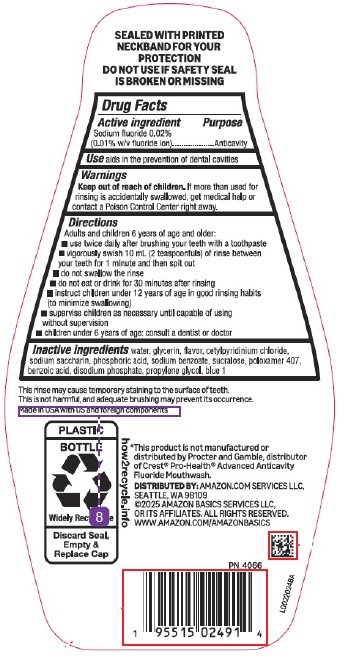 DRUG LABEL: Oral Antivavity
NDC: 72288-576 | Form: MOUTHWASH
Manufacturer: Amazon.Com Services LLC
Category: otc | Type: HUMAN OTC DRUG LABEL
Date: 20251211

ACTIVE INGREDIENTS: SODIUM FLUORIDE 0.1 mg/1 mL
INACTIVE INGREDIENTS: WATER; GLYCERIN; CETYLPYRIDINIUM CHLORIDE; SACCHARIN SODIUM; PHOSPHORIC ACID; SODIUM BENZOATE; SUCRALOSE; POLOXAMER 407; BENZOIC ACID; SODIUM PHOSPHATE, DIBASIC, ANHYDROUS; PROPYLENE GLYCOL; FD&C BLUE NO. 1

Basics 576.001/576AC-AD
Alcohol Free Fluoride Refreshing Mint Mouthwash

Tamper Evident Statement

SEALED WITH PRINTED NECKBAND FOR YOUR PROTECTION

DO NOT USE IF SAFETY SEAL IS BROKEN OR MISSING

Active ingredient

Sodium fluoride 0.02% (0.01% w/v fluoride ion)

Purpose

Anticavity

Use

aids in the prevention of dental cavities

Warnings

for this product

Keep out of reach of children.

If more than used for rinsing is accidentally swallowed, get medical help or contact a Poison Control Center right away.

Directions

Adults and children 6 years of age and older:

- use twice daily after brushing your teeth with a toothpaste
- vigorously swish 10 mL (2 teaspoonfuls) of rinse between your teeth for 1 minute and then spit out
- do not swallow the rinse
- do not eat or drink for 30 minutes after rinsing
- instruct children under 12 years of age in good rinsing habits (to minimize swallowing)
- supervise children as necessary until capable of using without supervision
- children under 6 years of age: consult a dentist or doctor

Inactive ingredients

water, glycerin, flavor, cetylpyridinium chloride, sodium saccharin, phosphoric acid, sodium benzoate, sucralose, poloxamer 407, benzoic acid, disodium phosphate, propylene glycol, blue 1

Disclaimers

This rinse may cause temporary staining to the surface of teeth.

This is not harmful, and adequate brushing may prevent its occurrence.

Made in USA with US and foreign components.

Disclaimer

*This product is not manufactured or distributed by Procter and Gamble, distributor of Crest®Pro-HealthAdvanced Anticavity Fluoride Mouthwash.

ADVERSE REACTION

DISTRIBUTED BY: Amazon.com, Services, LLC

Seattle, WA 98109

1-877-485-0385

©2025 Amazon Basics Services or its afiliates.

All rights reserved.

www.amazon.com/amazonbasics

PLASTIC BOTTLE

Widely Recyclable

Discard Seal, Empty & Replace Cap

how2recycle.info

PRINCIPAL DISPLAY PANEL

amazon basics

Refreshing Mint

Anticavity Fluoride Mouthwash

Alcohol Free

Refreshing Mint Flavor

Compare to Crest®Pro-Health®Advanced Anticavity Fluoride Mouthwash*

IMPORTANT: READ DIRECTIONS FOR PROPER USE.

33.8 FL OZ (1.05 QT) 1 L